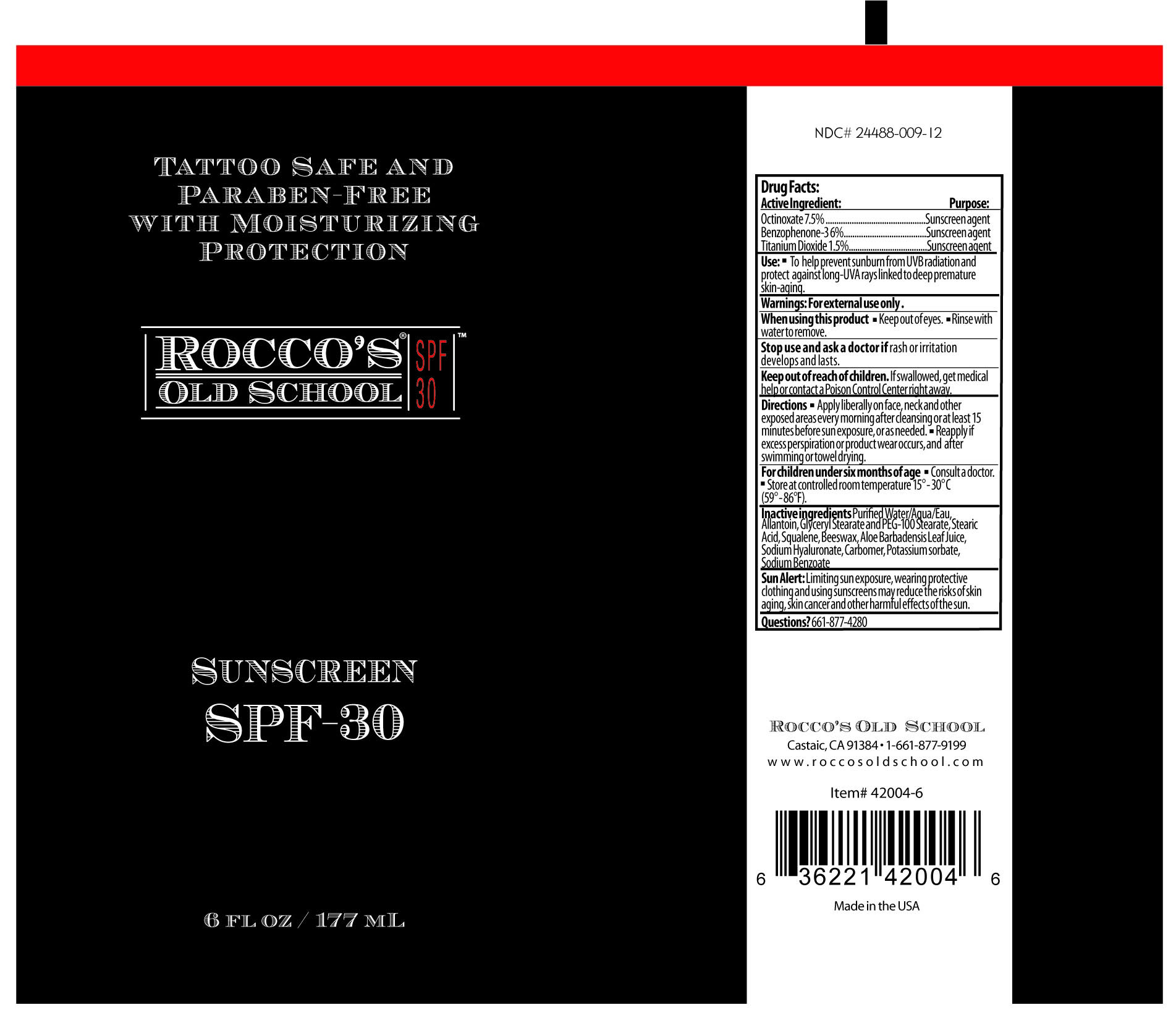 DRUG LABEL: Roccos Old School
NDC: 24488-009 | Form: CREAM
Manufacturer: Rocco's Old School
Category: otc | Type: HUMAN OTC DRUG LABEL
Date: 20110216

ACTIVE INGREDIENTS: OCTINOXATE 13.275 mL/177 mL; OXYBENZONE 10.62 mL/177 mL; TITANIUM DIOXIDE 2.655 mL/177 mL
INACTIVE INGREDIENTS: WATER; ALLANTOIN; GLYCERYL MONOSTEARATE; POLYOXYL 100 STEARATE; STEARIC ACID; SQUALENE; YELLOW WAX; ALOE VERA LEAF; HYALURONATE SODIUM; CARBOMER HOMOPOLYMER TYPE C; POTASSIUM SORBATE; SODIUM BENZOATE

Drug Facts

Active Ingredient

Octinoxate 7.5% ..............................................Sunscreen agent
Benzophenone-3 6%......................................Sunscreen agent
Titanium Dioxide 1.5%....................................Sunscreen agent

Use

- To help prevent sunburn from UVB radiation and
  protect against long-UVA rays linked to deep premature
  skin-aging.

Warnings

For external use only.

When using this product

- Keep out of eyes.
- Rinse with water to remove.

Stop use and ask doctor if

rash or irritation develops and lasts.

Keep out of reach of children.

If swallowed, get medical help or contact a Poison Control Center right away.

Directions

- Apply liberally on face, neck and other
  exposed areas every morning after cleansing or at least 15
  minutes before sun exposure, or as needed.
- Reapply if excess perspiration or product wear occurs, and after
  swimming or towel drying.
  For children under six months

For children under six months of age

- Consult a doctor.
- Store at controlled room temperature 15° - 30° C
  (59° - 86°F).

Inactive ingredients

Purified Water/Aqua/Eu, Allantoin,
Glyceryl Stearate and PEG-100 Stearate, Stearic Acid,
Squalene, Beeswax, Aloe Barbadensis Leaf Juice, Sodium
Hyaluronate, Carbomer, Potassium sorbate,
Sodium Benzoate

Sun Alert

Limiting sun exposure, wearing protective
clothing and using sunscreens may reduce the risks of skin
aging, skin cancer and other harmful effects of the sun.

Questions?

661-877-4280

PACKAGE LABEL

Place Holder Text